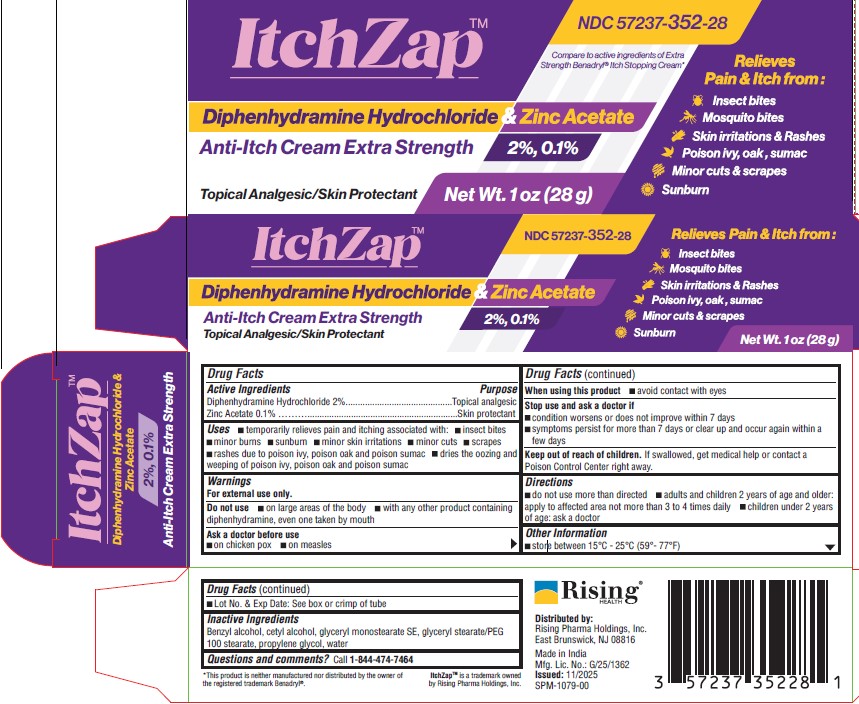 DRUG LABEL: ItchZap
NDC: 57237-352 | Form: CREAM
Manufacturer: Rising Pharma Holdings, Inc.
Category: otc | Type: HUMAN OTC DRUG LABEL
Date: 20251106

ACTIVE INGREDIENTS: DIPHENHYDRAMINE HYDROCHLORIDE 20 mg/1 g; ZINC ACETATE 1 mg/1 g
INACTIVE INGREDIENTS: BENZYL ALCOHOL; CETYL ALCOHOL; GLYCERYL MONOSTEARATE; GLYCERYL STEARATE/PEG-100 STEARATE; PROPYLENE GLYCOL; WATER

Diphenhydramine Hydrochloride 2% & Zinc Acetate 0.1% Anti-Itch Cream
Extra Strength

Drug Facts Active Ingredients

Diphenhydramine Hydrochloride 2%

Zinc Acetate 0.1%

Purpose

Topical analgesic

Skin protectant

Uses

- temporarily relieves pain and itching associated with: insect bites, minor burns, sunburn, minor skin irritations, minor cuts, scrapes, rashes due to poison ivy, poison oak and poison sumac
- dries the oozing and weeping of poison ivy, poison oak and poison sumac

Warnings

For external use only.

Do not use

- on large areas of the body
- with any other product containing diphenhydramine, even one taken by mouth

Ask a doctor before use

- on chicken pox
- on measles

When using this product

- avoid contact with eyes

Stop use and ask a doctor if

- condition worsens or does not improve within 7 days
- symptoms persists for more than 7 days or clear up and occur again within a few days

Keep out of reach of children.

If swallowed, get medical help or contact a Poison Control Center right away.

Directions

- do not use more than directed
- adults and children 2 years of age and older: apply to affected area not more than 3 to 4 times daily
- children under 2 years of age: ask a doctor

Other Information

- store between 15°C - 25°C (59°- 77°F)
- Lot No. & Exp Date: See box or crimp of tube

Inactive Ingredients

Benzyl alcohol, cetyl alcohol, glyceryl monostearate SE, glyceryl stearate/PEG 100 stearate, propylene glycol, water

Questions and comments?

Call 1-844-474-7464

ItchZapTM is a trademark owned by Rising Pharma Holdings, Inc.

Distributed by:

Rising Pharma Holdings, Inc.

East Brunswick, NJ 08816

Made in India

Mfg. Lic. No.: G/25/1362

Principal Display Panel

NDC 57237-352-28

ItchZapTM

Diphenhydramine Hydrochloride 2% & Zinc Acetate 0.1%

Anti-Itch Cream

Extra Strength

Topical Analgesic/Skin Protectant